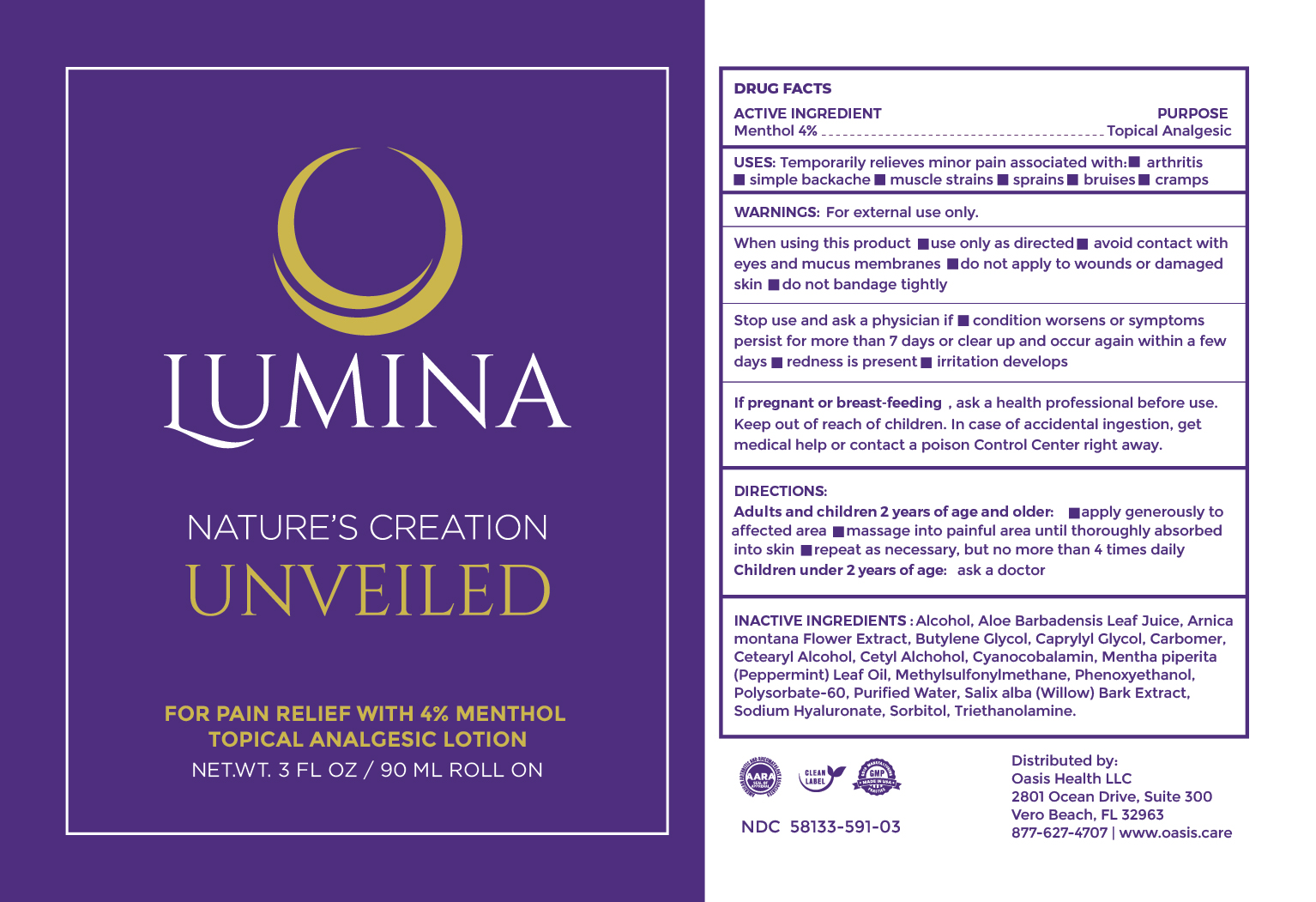 DRUG LABEL: LUMINA Natures Creation UNVEILED
NDC: 58133-591 | Form: CREAM
Manufacturer: Cosmetic Specialty Labs, Inc.
Category: otc | Type: HUMAN OTC DRUG LABEL
Date: 20230503

ACTIVE INGREDIENTS: MENTHOL 4 g/100 mL
INACTIVE INGREDIENTS: ALOE VERA LEAF; HYALURONATE SODIUM; CYANOCOBALAMIN; DIMETHYL SULFONE; ALCOHOL; ARNICA MONTANA FLOWER; BUTYLENE GLYCOL; CETOSTEARYL ALCOHOL; PHENOXYETHANOL; CARBOMER 940; SALIX ALBA BARK; SORBITOL; TROLAMINE; CETYL ALCOHOL; PEPPERMINT OIL; POLYSORBATE 60; CAPRYLYL GLYCOL; WATER

Active Incredient

Menthol, 4%

Purpose

Topical analgesic

Uses

temporarily relieves minor pain associated with: • arthritis • simple backache • muscle strains • sprains • bruises • cramps

Warnings

For external use only

WHEN USING

When using this prodcut•use only as directed •avoid contact with eyes or mucous membranes •do not apply to wounds or damaged skin •do not bandage tightly

Stop use and ask a physician if•condition worsens or symptoms persist for more than 7 days or clear up and occur again within a few days •redness is present •irritation develops

KEEP OUT OF REACH OF CHILDREN

If pregnant or breast-feeding, ask a health professional before use.

Keep out of reach of children . If case of accidental ingestion, get medical help or contact a poison Control Center right away.

Directions:

Adults and children 2 years of age and older:•apply generously to affected area •massage into painful area until thoroughly absorbed into skin •repeat as necessary, but no more than 4 time daily

Children under 2 years of age: ask a doctor

RECENT MAJOR CHANGES

effective date update and wording of Directions for Use updated to match label

Inactive ingredients

Alcohol, Aloe Barbadensis Leaf Juice, Arnica montana Flower Extract, Butylene Glycol, Caprylyl Glycol, Carbomer, Cetearyl Alcohol, Cetyl Alcohol, Cyanocobalamin, Mentha piperita (Peppermint) Leaf Oil, Methylsulfonylmethane, Phenoxyethanol, Polysorbate-60, Purified Water, Salix alba (Willow) Bark Extract, Sodium Hyaluronate, Sorbitol, Triethanolamine